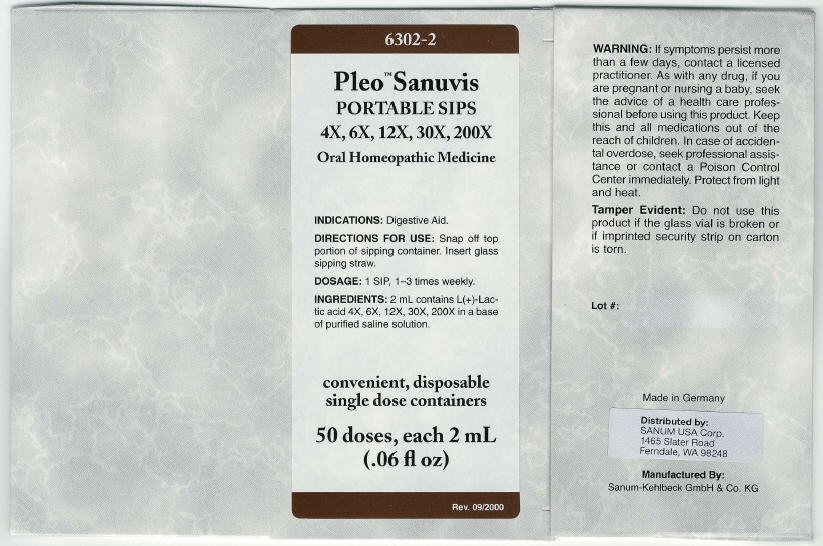 DRUG LABEL: Pleo Sanuvis
NDC: 60681-6302 | Form: KIT | Route: ORAL
Manufacturer: Sanum Kehlbeck GmbH & Co. KG
Category: homeopathic | Type: HUMAN OTC DRUG LABEL
Date: 20091120

ACTIVE INGREDIENTS: lactic acid, l- 4 [hp_X]/2 mL; lactic acid, l- 6 [hp_X]/2 mL; lactic acid, l- 12 [hp_X]/2 mL; lactic acid, l- 30 [hp_X]/2 mL; lactic acid, l- 200 [hp_X]/2 mL
INACTIVE INGREDIENTS: water; sodium chloride; water; sodium chloride; water; sodium chloride; water; sodium chloride; water; sodium chloride

Pleo™ Sanuvis
PORTABLE SIPS
4X, 6X, 12X, 30X, 200X

Oral Homeopathic Medicine

50 doses, each 2 mL
(.06 fl oz)

INDICATIONS

Digestive Aid.

DIRECTIONS FOR USE

Snap off top portion of sipping container. Insert glass sipping straw.

DOSAGE

1 SIP, 1–3 times weekly.

INGREDIENTS

2 mL contains L(+)-Lactic acid 4X, 6X, 12X, 30X, 200X in a base of purified saline solution.

WARNING

If symptoms persist more than a few days, contact a licensed practitioner. As with any drug, if you are pregnant or nursing a baby, seek the advice of a health care professional before using this product.

KEEP OUT OF REACH OF CHILDREN

Keep this and all medications out of the reach of children. In case of accidental overdose, seek professional assistance or contact a Poison Control Center immediately.

STORAGE AND HANDLING

Protect from light and heat.

Tamper Evident

Do not use this product if the glass vial is broken or if imprinted security strip on carton is torn.

Made in Germany

Distributed by:
SANUM USA Corp.
1465 Slater Road
Ferndale, WA 98248

Manufactured By:
Sanum-Kehlbeck GmbH & Co. KG

Rev. 09/2000

PRINCIPAL DISPLAY PANEL - 2 mL Carton

6302-2

Pleo™ Sanuvis
PORTABLE SIPS
4X, 6X, 12X, 30X, 200X

Oral Homeopathic Medicine

INDICATIONS: Digestive Aid.

DIRECTIONS FOR USE: Snap off top
portion of sipping container. Insert glass
sipping straw.

DOSAGE: 1 SIP, 1–3 times weekly.

INGREDIENTS: 2 mL contains L(+)-Lac-
tic acid 4X, 6X, 12X, 30X, 200X in a base
of purified saline solution.

convenient, disposable
single dose containers

50 doses, each 2 mL
(.06 fl oz)

Rev. 09/2000